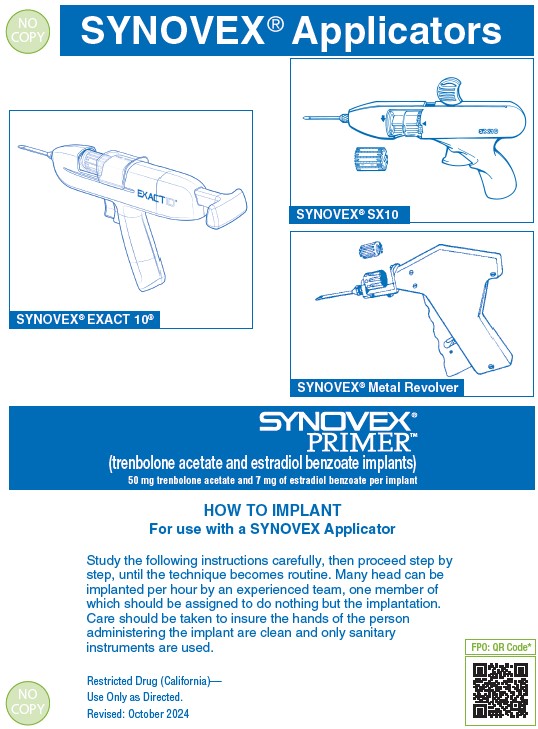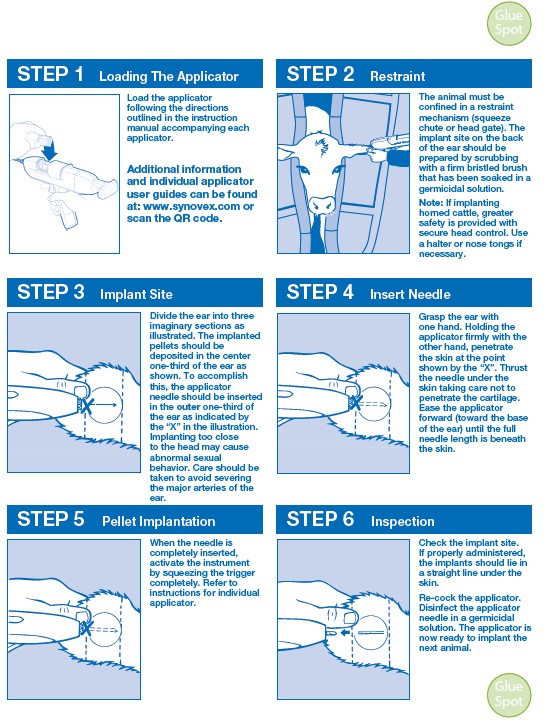 DRUG LABEL: Synovex Primer
NDC: 54771-6870 | Form: IMPLANT
Manufacturer: Zoetis Inc.
Category: animal | Type: OTC ANIMAL DRUG LABEL
Date: 20250221

ACTIVE INGREDIENTS: TRENBOLONE ACETATE 50 mg/1 1; ESTRADIOL BENZOATE 7 mg/1 1

SYNOVEX Primer®

SYNOVEX Primer®
(trenbolone acetate and estradiol benzoate implants)
50 mg trenbolone acetate and 7 mg of estradiol benzoate per implant
SUBCUTANEOUS IMPLANTS FOR GROWING BEEF STEERS AND HEIFERS ON PASTURE AND IN A DRY LOT

DESCRIPTION

SYNOVEX® PRIMER™ (trenbolone acetate and estradiol benzoate implants) is a growth promoting implant containing 50 mg of trenbolone acetate and 7 mg of estradiol benzoate per implant. Each implant consists of 2 pellets. Ten implants are provided in each cartridge.

WITHDRAWAL PERIODS AND RESIDUE WARNINGS

No withdrawal period is required when used according to labeling.
Do not use in beef calves less than 2 months of age, dairy calves, and veal calves. A withdrawal period has not been established for this product in pre-ruminating calves.
Do not use in dairy cows or in animals intended for subsequent breeding. Use in these cattle may cause drug residues in milk and/or in calves born to these cows.
Implant pellets subcutaneously in ear only. Any other location is a violation of Federal law. Do not attempt salvage of implanted site for human or animal food.

USER SAFETY WARNINGS

Not for use in humans. Keep out of reach of children.

ANIMAL SAFETY WARNINGS

Bulling has occasionally been reported in implanted steers and heifers. Vaginal and rectal prolapse, udder development, ventral edema and elevated tailheads have occasionally been reported in heifers administered SYNOVEX® PRIMER™ implants.

DIRECTIONS

Administer one SYNOVEX® PRIMER™ implant (two pellets), containing 50 mg of trenbolone acetate and 7 mg of estradiol benzoate, to each steer or heifer by subcutaneous implantation in the middle-third of the ear.
Use only a SYNOVEX applicator. Approved implantation technique is fully described in the fold-out carton section. Never sacrifice careful, clean technique for speed of implantation.

STORAGE

Store unopened product at controlled room temperature 20°-25°C (68°-77°F) with excursions between 15°-30°C (59°-86°F). Avoid excessive heat and humidity. Use product before the expiration date on the label.
Once the pouch is opened, unused product may be stored in the end-folded pouch (away from light) for up to six months under refrigerated conditions 2°-8°C (36°-47°F) or at room temperature 20°-25°C (68°-77°F) with excursions between 15°-30°C (59°-86°F) for up to one month.

DISPOSAL

SYNOVEX® PRIMER™ waste materials should be disposed of according to prescribed Federal, State, and Local guidelines.

INDICATIONS FOR USE

• For increased rate of weight gain in growing beef steers and heifers on pasture (stocker, feeder, and slaughter).
• For increased rate of weight gain in growing beef steers and heifers in a dry lot.^1
• This implant is not approved for repeated implantation (reimplantation) with this or any other cattle ear implant
in growing beef steers and heifers on pasture or in a dry lot as safety and effectiveness have not been evaluated.
Do not use in beef calves less than 2 months of age, dairy calves, and veal calves because effectiveness and safety have not been established.
Do not use in animals intended for subsequent breeding, or in dairy cows.
^1CVM Appendix III of GFI 191, August 27, 2020, https://www.fda.gov/animal-veterinary/new-animal-drugapplications/
classes-major-food-producing-animals-newanimal-drug-applications#beef

QUESTIONS/COMMENTS?

For a copy of the Safety Data Sheet or to report side effects, contact Zoetis Inc. at 1-888-963-8471. For additional information about reporting side effects for animal drugs, contact FDA at 1-888-FDA-VETS or http://www.fda.gov/reportanimalae.

Manufactured By A Non-Sterilizing Process
Restricted Drug (California)—Use Only As Directed.

IMPORTANT

Read ALL sides of carton

Approved by FDA under NADA # 141-043
NET CONTENTS: 10 CARTRIDGES
Each Cartridge Contains 10 implants (100 implants total)
zoetis
Distributed by:
Zoetis Inc.
Kalamazoo, MI 49007
40044978

PRINCIPAL DISPLAY PANEL - 10 Cartridge Implant Carton

40049311